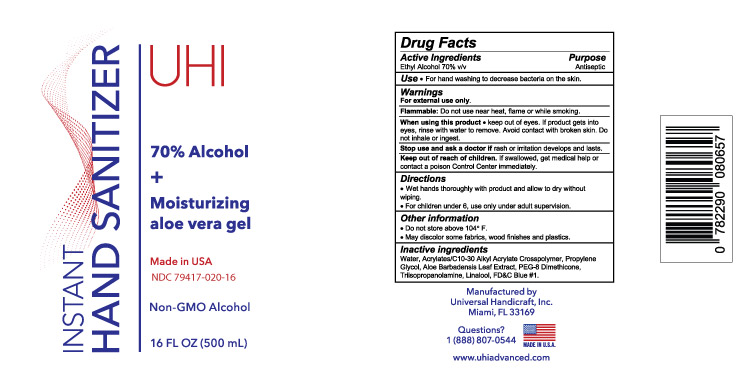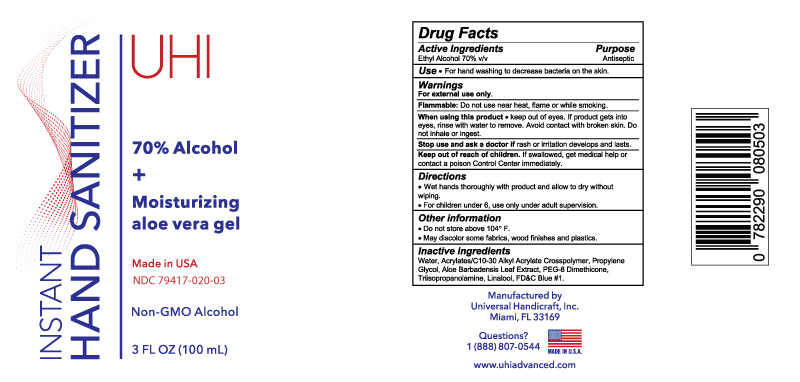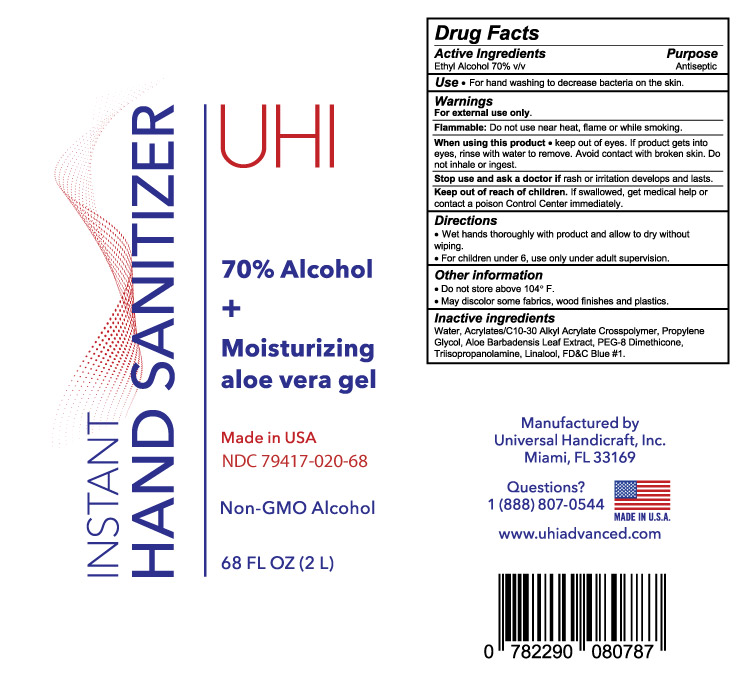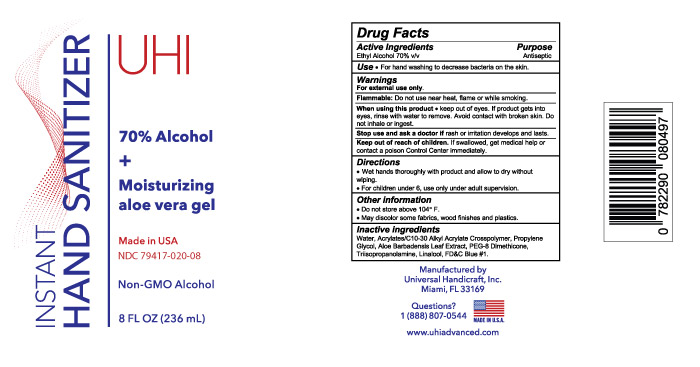 DRUG LABEL: UHI Hand Sanitizer
NDC: 79417-020 | Form: GEL
Manufacturer: Kova Laboratories, Inc.
Category: otc | Type: HUMAN OTC DRUG LABEL
Date: 20200804

ACTIVE INGREDIENTS: ALCOHOL 70 L/100 L
INACTIVE INGREDIENTS: WATER 28.397 L/100 L; ALOE VERA LEAF 0.05 L/100 L; LINALOOL, (+/-)- 0.07 L/100 L; CARBOMER 1342 0.27 L/100 L; PROPYLENE GLYCOL 0.5 L/100 L; PEG-8 DIMETHICONE 0.3 L/100 L; TRIISOPROPANOLAMINE 0.41 L/100 L; FD&C BLUE NO. 1 0.003 L/100 L

Active Ingredient(s)

Ethyl Alcohol 70% v/v

Purpose

Antiseptic, Hand Sanitizer

Use

For hand washing to decrease bacteria on the skin

Warnings

For external use only. Flammable. Do not use near heat, flame or while smoking.

Do not use

- in children less than 2 months of age
- on open skin wounds

When using this product keep out of eyes. if product gets into eyes, rinse with water to remove. Avoid contact with broken skin. Do not inhale or ingest.

Stop use and ask a doctor if rash or irritation develops and lasts.

Keep out of reach of children. If swallowed, get medical help or contact a Poison Control Center immediately

Directions

- Place enough product on hands to cover all surfaces. Rub hands together until dry.
- Supervise children under 6 years of age when using this product to avoid swallowing.

Other information

Do not store above 104F

May discolor some fabrics, wood finishes, and plastics

Inactive ingredients

Water, Acrylates/C10-30 Alkyl Acrylate Crosspolymer, Propylene Glycol, Aloe Barbadensis Leaf Extract, PEG-8 Dimethicone, Triisopropanolamine, Linalool, FD&C Blue #1